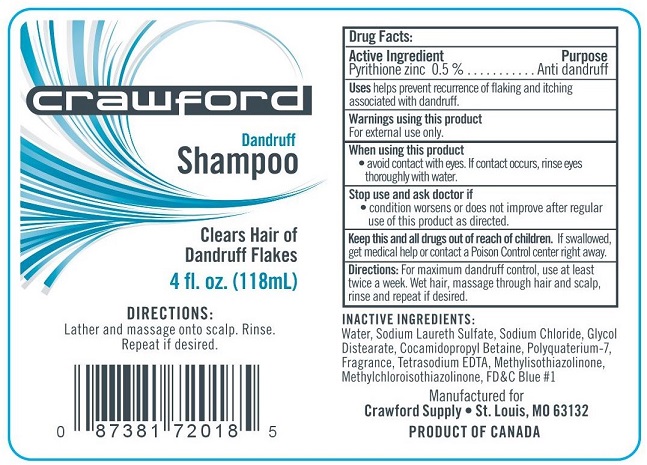 DRUG LABEL: Crawford Dandruff
NDC: 50157-009 | Form: SHAMPOO
Manufacturer: Brands International
Category: otc | Type: HUMAN OTC DRUG LABEL
Date: 20191218

ACTIVE INGREDIENTS: PYRITHIONE ZINC 0.5 g/100 mL
INACTIVE INGREDIENTS: WATER; SODIUM LAURETH SULFATE; GLYCOL DISTEARATE; SODIUM CHLORIDE; COCAMIDOPROPYL BETAINE; POLYQUATERNIUM-7 (70/30 ACRYLAMIDE/DADMAC; 1600 KD); EDETATE SODIUM; METHYLCHLOROISOTHIAZOLINONE; METHYLISOTHIAZOLINONE; FD&C BLUE NO. 1

Crawford Dandruff Shampoo

Drug Facts

Active Ingredient

Pyrithione zinc 0.5%

Purpose

Anti dandruff

Uses

helps prevent recurrence of flaking and itching associated with dandruff.

Warnings using this product
For external use only.

KEEP OUT OF REACH OF CHILDREN

Keep this and all drugs out of reach of children. If swallowed, get medical help or contact a Poison Control Center right away.

DOSAGE AND ADMINISTRATION

Directions: For maximum dandruff control, use at least twice a week. Wet hair, massage through hair and scalp, rinse and repeat if desired.

INACTIVE INGREDIENTS:

Water (Aqua), Sodium Laureth Sulfate, Sodium Chloride, Glycol Distearate, Cocamidopropyl Betaine, Polyquaternium-7, Fragrance, Tetrasodium EDTA, Methylchloroisothiazolinone, Methylisothiazolinone, FD&C Blue #1

Manufactured for

Crawford Supply • St. Louis, MO 63132

PRODUCT OF CANADA

PACKAGE LABEL

Crawford

Dandruff Shampoo

Clears Hair of Dandruff Flakes

4 fl. oz. (118 mL)